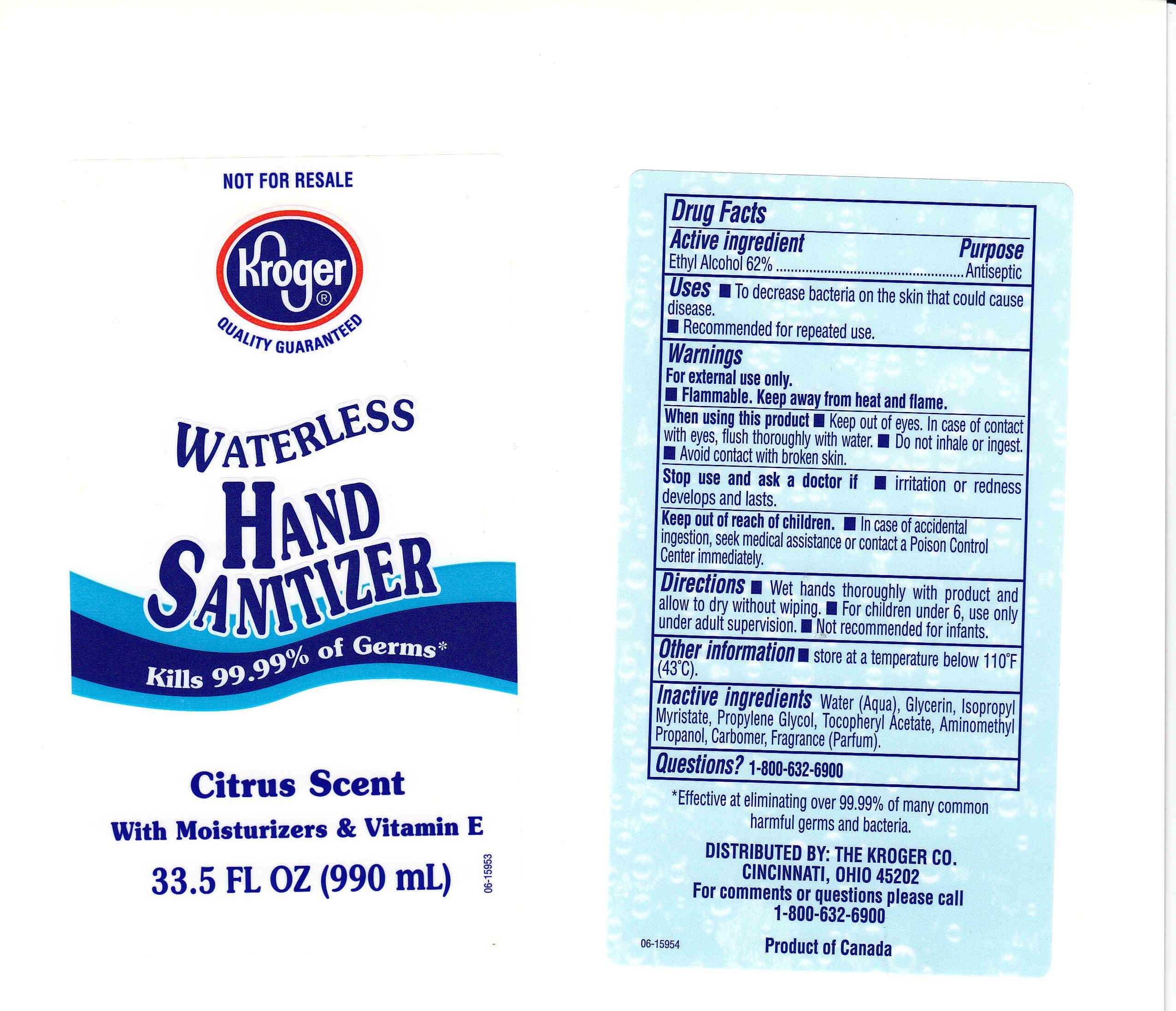 DRUG LABEL: WATERLESS HAND SANITIZER
NDC: 30142-231 | Form: GAS
Manufacturer: THE KROGER COMPANY
Category: otc | Type: HUMAN OTC DRUG LABEL
Date: 20110405

ACTIVE INGREDIENTS: ALCOHOL 62 mL/100 mL
INACTIVE INGREDIENTS: WATER; GLYCERIN; ISOPROPYL MYRISTATE; PROPYLENE GLYCOL; .ALPHA.-TOCOPHEROL ACETATE, D-; AMINOMETHYLPROPANOL; CARBOMER 934

DRUG FACTS

ACTIVE INGREDIENT

ETHYL ALCOHOL 62 PERCENT

PURPOSE

ANTISEPTIC

USES

TO DECREASE BACTERIA ON THE SKIN THAT COULD CAUSE DISEASE. RECOMMENDED FOR REPEATED USE.

WARNINGS

FOR EXTERNAL USE ONLY.

FLAMMABLE. KEEP AWAY FROM HEAT AND FLAME.

WHEN USING THIS PRODUCT

KEEP OUT OF EYES. IN CASE OF CONTACT WITH EYES, FLUSH THOROUGHLY WITH WATER. DO NOT INHALE OR INGEST. AVOID CONTACT WITH BROKEN SKIN.

STOP AND ASK A DOCTOR IF

IRRITATION OR REDNESS DEVELOPS AND LASTS.

KEEP OUT OF REACH OF CHILDREN

IN CASE OF ACCIDENTAL INGESTION, SEEK MEDICAL ASSISTANCE OR CONTACT A POISON CONTROL CENTER IMMEDIATELY.

DIRECTIONS

WET HANDS THOROUGHLY WITH PRODUCT AND ALLOW TO DRY WITHOUT WIPING. FOR CHILDREN UNDER 6, USE ONLY UNDER ADULT SUPERVISION. NOT RECOMMENDED FOR INFANTS.

OTHER INFORMATION

STORE AT A TEMPERATURE BELOW 110 DEGREES FAHRENHEIT (43 DEGREES CELSIUS).

INACTIVE INGREDIENTS

WATER, GLYCERIN, ISOPROPYL MYRISTATE, PROPYLENE GLYCOL, TOCOPHERYL ACETATE, AMINOMETHYL PROPANOL, CARBOMER, FRAGRANCE.

QUESTIONS OR COMMENTS

1-800-632-6900